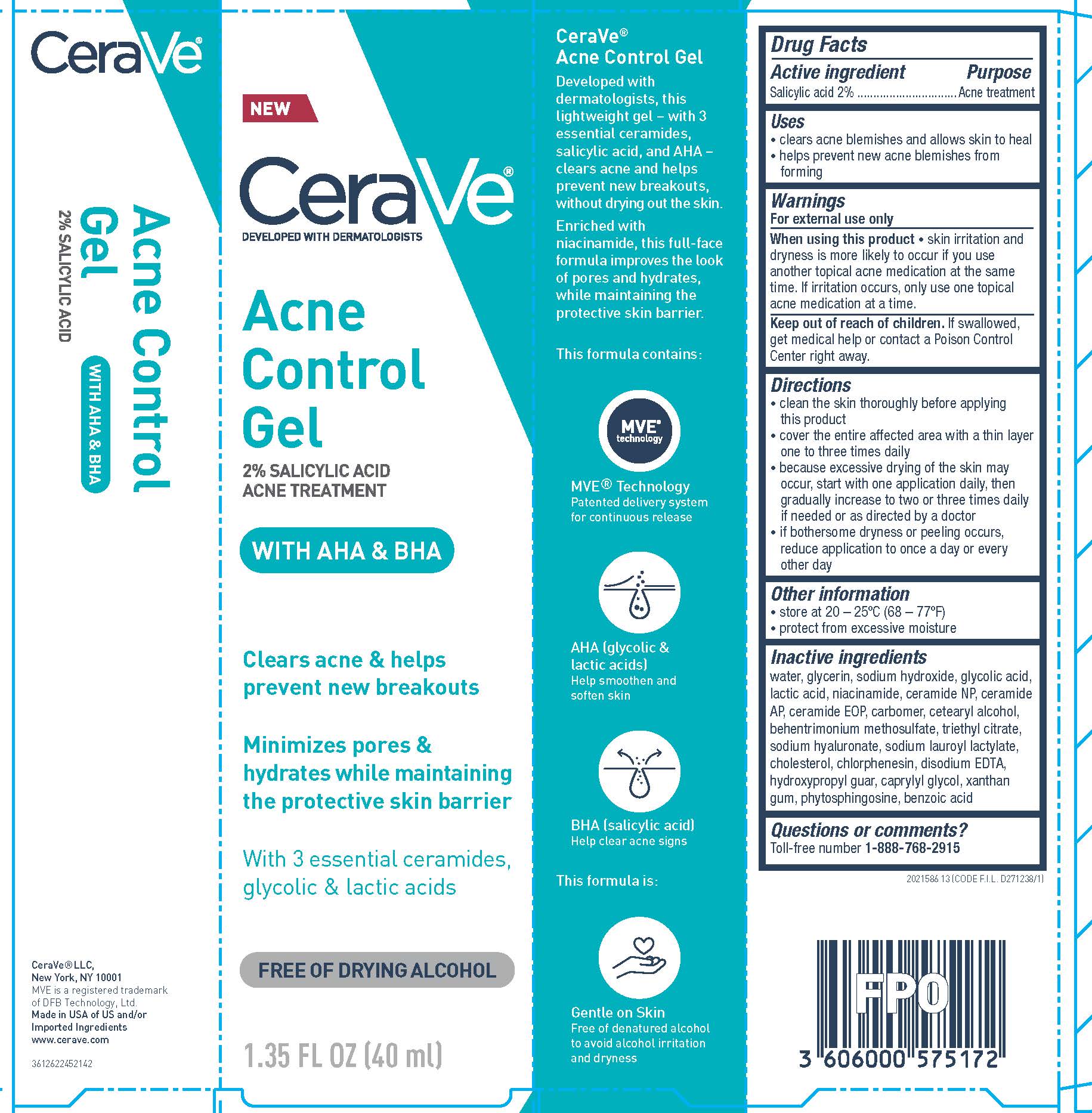 DRUG LABEL: CeraVe Developed with Dermatologists Acne Control Acne Treatment
NDC: 49967-172 | Form: GEL
Manufacturer: L'Oreal USA Products Inc
Category: otc | Type: HUMAN OTC DRUG LABEL
Date: 20231231

ACTIVE INGREDIENTS: Salicylic Acid 20 mg/1 mL
INACTIVE INGREDIENTS: WATER; GLYCERIN; SODIUM HYDROXIDE; GLYCOLIC ACID; LACTIC ACID; NIACINAMIDE; CERAMIDE NP; CERAMIDE AP; CERAMIDE 1; CARBOMER HOMOPOLYMER, UNSPECIFIED TYPE; CETOSTEARYL ALCOHOL; BEHENTRIMONIUM METHOSULFATE; TRIETHYL CITRATE; HYALURONATE SODIUM; SODIUM LAUROYL LACTYLATE; CHOLESTEROL; CHLORPHENESIN; EDETATE DISODIUM; GUARAPROLOSE (1300 MPA.S AT 1%); CAPRYLYL GLYCOL; XANTHAN GUM; PHYTOSPHINGOSINE; BENZOIC ACID

Drug Facts

Active ingredient

Salicylic acid 2%

Purpose

Acne treatment

Uses

- clears acne blemishes and allows skin to heal
- helps prevent new acne blemishes from forming

Warnings

For external use only

When using this product

skin irritation and dryness is more likely to occur if you use another topical acne medication at the same time. if irritation occurs, only use one topical acne medication at a time.

Keep out of reach of children.

If swallowed, get medical help or contact a Poison Control Center right away.

Directions

• clean the skin thoroughly before applying this product
• cover the entire affected area with a thin layer one to three times daily
• because excessive drying of the skin may occur, start with one application daily, then gradually increase to two or three times daily if needed or as directed by a doctor
• if bothersome dryness or peeling occurs, reduce application to once a day or every other day

Other information

• store at 20 – 25ºC (68 – 77ºF)
• protect from excessive moisture

Inactive ingredients

water, glycerin, sodium hydroxide, glycolic acid, lactic acid, niacinamide, ceramide NP, ceramide AP, ceramide EOP, carbomer, cetearyl alcohol, behentrimonium methosulfate, triethyl citrate, sodium hyaluronate, sodium lauroyl lactylate, cholesterol, chlorphenesin, disodium EDTA, hydroxypropyl guar, caprylyl glycol, xanthan gum, phytosphingosine, benzoic acid